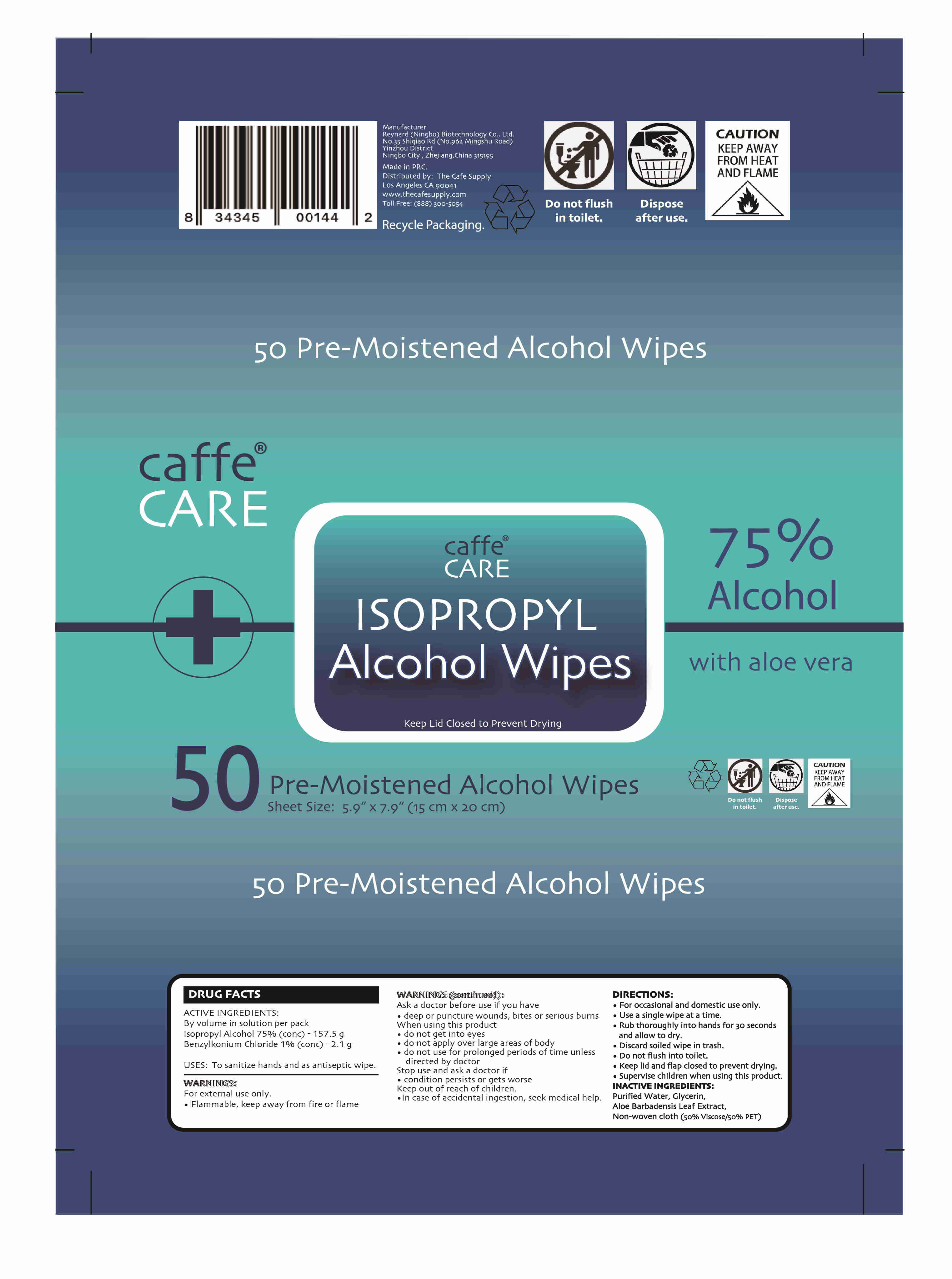 DRUG LABEL: ISOPROPYL Alcohol Wipes
NDC: 55485-005 | Form: CLOTH
Manufacturer: Reynard (Ningbo) Biotechnology Co., Ltd.
Category: otc | Type: HUMAN OTC DRUG LABEL
Date: 20220420

ACTIVE INGREDIENTS: BENZALKONIUM CHLORIDE 2.1 g/50 1; ISOPROPYL ALCOHOL 157.5 g/50 1
INACTIVE INGREDIENTS: ALOE; GLYCERIN; WATER

DOSAGE AND ADMINISTRATION

Store in a cool and dry place

INACTIVE INGREDIENT

Purified Water, non-woven cloth, Aloe Extract, Glycerin

INDICATIONS AND USAGE

●For occasional and domestic use only.
●Use a single wipe at a time.
●Rub thoroughly into hands for 30 seconds and allow to dry.
●Discard soiled wipe in trash.
●DO not flush into toilet.
●Keep lid and flap closed to prevent drying.
●Supervise children when using this product.

ACTIVE INGREDIENT

Isopropyl alcohol

Benzalkonium Chloride

keep out of reach of children

PURPOSE

Disinfection
Sterilization
No Rinseing

WARNINGS

For external use only.
●Flammable, keep away from fire or flame Ask a doctor before use if you have
●deep or puncture wounds, bites or serious burns When using this product
●do not get into eyes
●do not apply over large areas of body
●do not use for prolonged periods of time unless directed by doctor